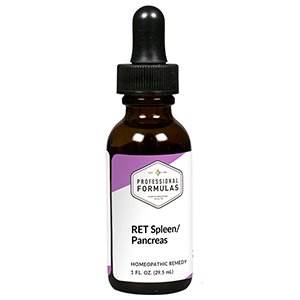 DRUG LABEL: RET Spleen/Pancreas
NDC: 63083-7002 | Form: LIQUID
Manufacturer: Professional Complementary Health Formulas
Category: homeopathic | Type: HUMAN OTC DRUG LABEL
Date: 20190815

ACTIVE INGREDIENTS: CENTAURIUM ERYTHRAEA FLOWERING TOP 3 [hp_X]/29.5 mL; LARIX DECIDUA FLOWERING TOP 3 [hp_X]/29.5 mL; POTASSIUM PHOSPHATE, UNSPECIFIED FORM 3 [hp_X]/29.5 mL; SILICON DIOXIDE 3 [hp_X]/29.5 mL; SEMECARPUS ANACARDIUM JUICE 30 [hp_X]/29.5 mL; BRYONIA ALBA ROOT 30 [hp_X]/29.5 mL; LYCOPODIUM CLAVATUM SPORE 30 [hp_X]/29.5 mL
INACTIVE INGREDIENTS: ALCOHOL; WATER

RET2

ACTIVE INGREDIENTS

Centaury flower essence 3X
Larch flower essence 3X
Kali phosphoricum 3X, 6X, 30X
Silicea 3X, 6X, 30X
Anacardium orientale 30X, 100X, 200X
Bryonia 30X, 100X, 200X
Lycopodium clavatum 30X, 100X, 200X

QUESTIONS

Professional Formulas

PO Box 2034 Lake Oswego, OR 97035

INDICATIONS

Temporarily relieves lack of confidence, discouragement, inferiority, sadness, passiveness, dread, anxiousness, or oversensitivity.*

PURPOSE

*Claims based on traditional homeopathic practice, not accepted medical evidence. Not FDA evaluated.

WARNINGS

In case of overdose, get medical help or contact a poison control center right away.

Keep out of the reach of children.

PREGNANCY OR BREAST FEEDING

If pregnant or breastfeeding, ask a healthcare professional before use.

DIRECTIONS

Place drops under tongue 30 minutes before/after meals. Adults and children 12 years and over: Take 5 drops up to 4 times per day for up to one month. Consult a physician for use in children under 12 years of age.

OTHER INFORMATION

Tamper resistant. If seal is broken, do not use. After opening, close container tightly and store at room temperature away from heat.

INACTIVE INGREDIENTS

20% ethanol, purified water.

LABEL

Est 1985

Professional Formulas

Complementary Health

RET Spleen/Pancreas

Homeopathic Remedy

1 FL. OZ. (29.5 mL)